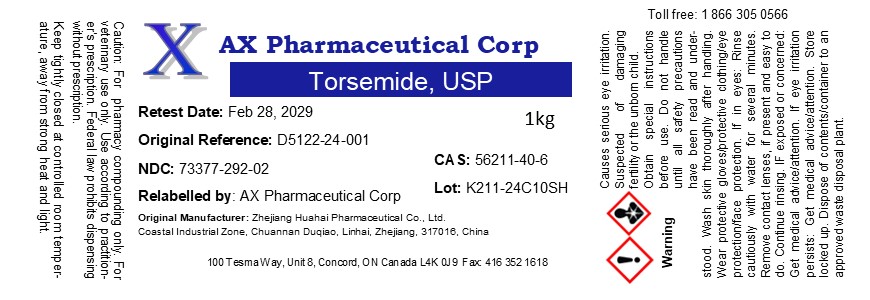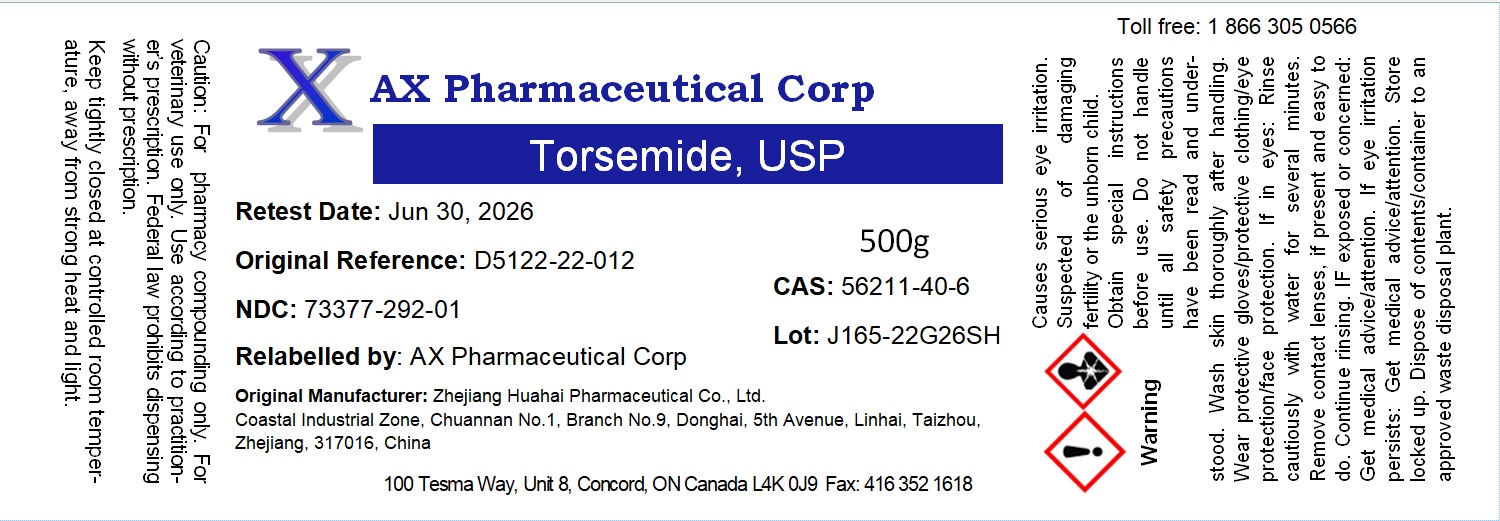 DRUG LABEL: Torsemide
NDC: 73377-292 | Form: POWDER
Manufacturer: AX Pharmaceutical Corp
Category: other | Type: BULK INGREDIENT - ANIMAL DRUG
Date: 20250905

ACTIVE INGREDIENTS: TORSEMIDE 1 g/1 g

Torsemide